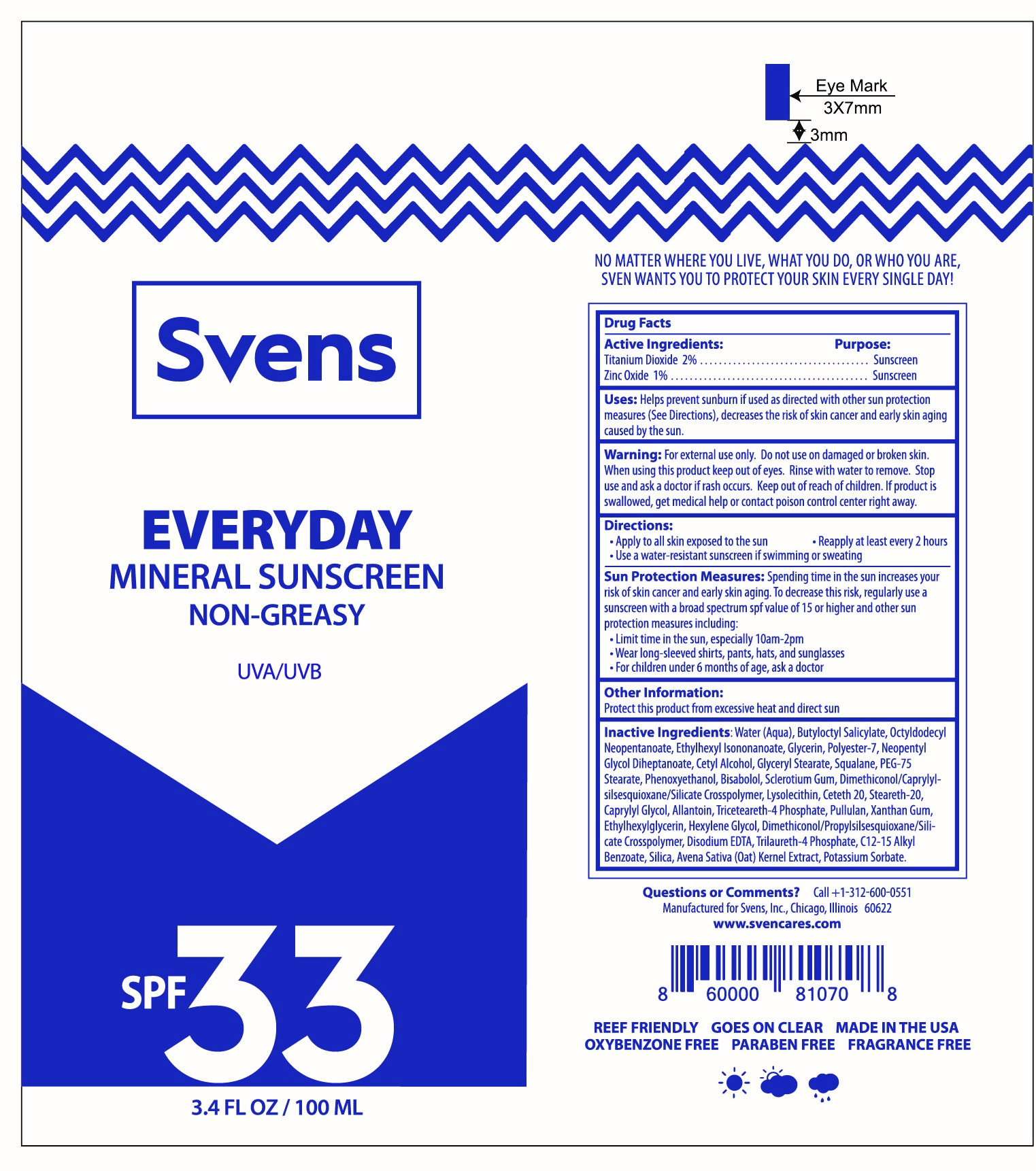 DRUG LABEL: Svens Everyday Mineral Sunscreen
NDC: 72743-4314 | Form: LOTION
Manufacturer: Svens, Inc
Category: otc | Type: HUMAN OTC DRUG LABEL
Date: 20251114

ACTIVE INGREDIENTS: TITANIUM DIOXIDE 22 mg/1 mL; ZINC OXIDE 11 mg/1 mL
INACTIVE INGREDIENTS: CAPRYLYL GLYCOL; HEXYLENE GLYCOL; POTASSIUM SORBATE; PULLULAN; STEARETH-20; .ALPHA.-BISABOLOL, (+)-; ALLANTOIN; CETYL ALCOHOL; NEOPENTYL GLYCOL DIHEPTANOATE; PHENOXYETHANOL; SILICON DIOXIDE; AVENA SATIVA WHOLE; POLYESTER-7; BUTYLOCTYL SALICYLATE; GLYCERIN; WATER; TRICETEARETH-4 PHOSPHATE; XANTHAN GUM; ETHYLHEXYLGLYCERIN; TRILAURETH-4 PHOSPHATE; C12-20 ALKYL BENZOATE; OCTYLDODECYL NEOPENTANOATE; ETHYLHEXYL ISONONANOATE; SQUALANE; DIMETHICONOL/PROPYLSILSESQUIOXANE/SILICATE CROSSPOLYMER (450000000 MW)

Svens Everyday Mineral Sunscreen